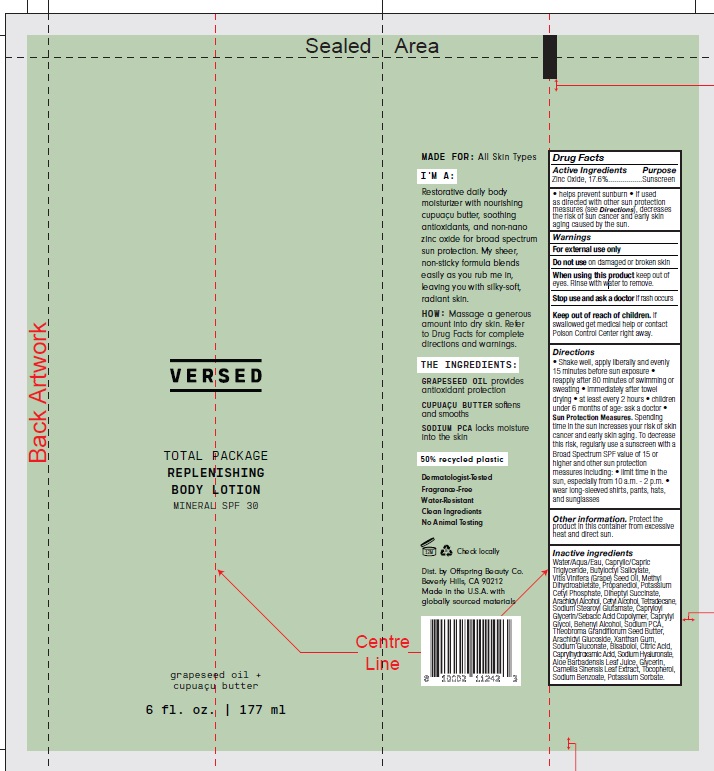 DRUG LABEL: Versed SPF 30 Replenishing Body Mineral
NDC: 73690-028 | Form: LOTION
Manufacturer: Offspring Beauty Co.
Category: otc | Type: HUMAN OTC DRUG LABEL
Date: 20241220

ACTIVE INGREDIENTS: ZINC OXIDE 17.6 g/100 mL
INACTIVE INGREDIENTS: TETRADECANE; ARACHIDYL GLUCOSIDE; POTASSIUM CETYL PHOSPHATE; GREEN TEA LEAF; SODIUM BENZOATE; HYALURONATE SODIUM; GRAPE SEED OIL; POTASSIUM SORBATE; SODIUM STEAROYL GLUTAMATE; CITRIC ACID MONOHYDRATE; CAPRYLHYDROXAMIC ACID; DOCOSANOL; CETYL ALCOHOL; PROPANEDIOL; GLYCERIN; XANTHAN GUM; DIHEPTYL SUCCINATE; CAPRYLOYL GLYCERIN/SEBACIC ACID COPOLYMER (2000 MPA.S); MEDIUM-CHAIN TRIGLYCERIDES; CAPRYLYL GLYCOL; LEVOMENOL; SODIUM GLUCONATE; WATER; ARACHIDYL ALCOHOL; TOCOPHEROL; ALOE VERA LEAF; BUTYLOCTYL SALICYLATE; THEOBROMA GRANDIFLORUM SEED BUTTER; METHYL DIHYDROABIETATE; SODIUM PYRROLIDONE CARBOXYLATE

Versed - SPF 30 Mineral Body Lotion (16-MK-055)

Active Ingredient

Zinc Oxide - 17.6%

Purpose

Sunscreen

PURPOSE

Sunscreen

Uses

• Helps prevent sunburn

• If used as directed with other sun protection measures (see Directions), decreases the risk of skin cancer and early skin aging caused by the sun

Warnings

- For external use only
- Do not use on damaged or broken skin
- When using this product keep out of eyes. Rinse with water to remove.
- Stop use and ask a doctor if rash occurs

Keep out of reach of children. If swallowed, get medical help or contact a Poison Control Center right away.

Directions

- Shake well, apply liberally and evenly 15 minutes before sun exposure
- Reapply after 80 minutes of swimming or sweating. Immediately after towel drying. At least every 2 hours.
- Children under 6 months of age: ask a doctor
- Sun Protection Measures. Spending time in the sun increases your risk of skin cancer and early skin aging. To decrease this risk, regularly use a sunscreen with a Broad Spectrum SPF value of 15 or higher and othe sun protection measures including: limit time in sun, especially from 10 a.m. to 2 p.m. and wear long-sleeved shirts, pants, hats, and sunglasses

Other information

Protect this product in this container from excessive heat and direct sun.

INACTIVE INGREDIENT

Water/Aqua/Eau, Caprylic/Capric Triglyceride, Butyloctyl Salicylate, Vitis Vinifera (Grape) Seed Oil, Methyl Dihydroabietate, Propanediol, Potassium Cetyl Phosphate, Diheptyl Succinate, Arachidyl Alcohol, Cetyl Alcohol, Tetradecane, Sodium Stearoyl Glutamate, Capryloyl Glycerin/Sebacic Acid Copolymer, Caprylyl Glycol, Behenyl Alcohol, Sodium PCA, Theobroma Grandiflorum Seed Butter, Arachidyl Glucoside, Xanthan Gum, Sodium Gluconate, Bisabolol, Citric Acid, Caprylhydroxamic Acid, Sodium Hyaluronate, Aloe Barbadensis Leaf Juice, Glycerin, Camellia Sinensis Leaf Extract, Tocopherol, Sodium Benzoate, Potassium Sorbate.